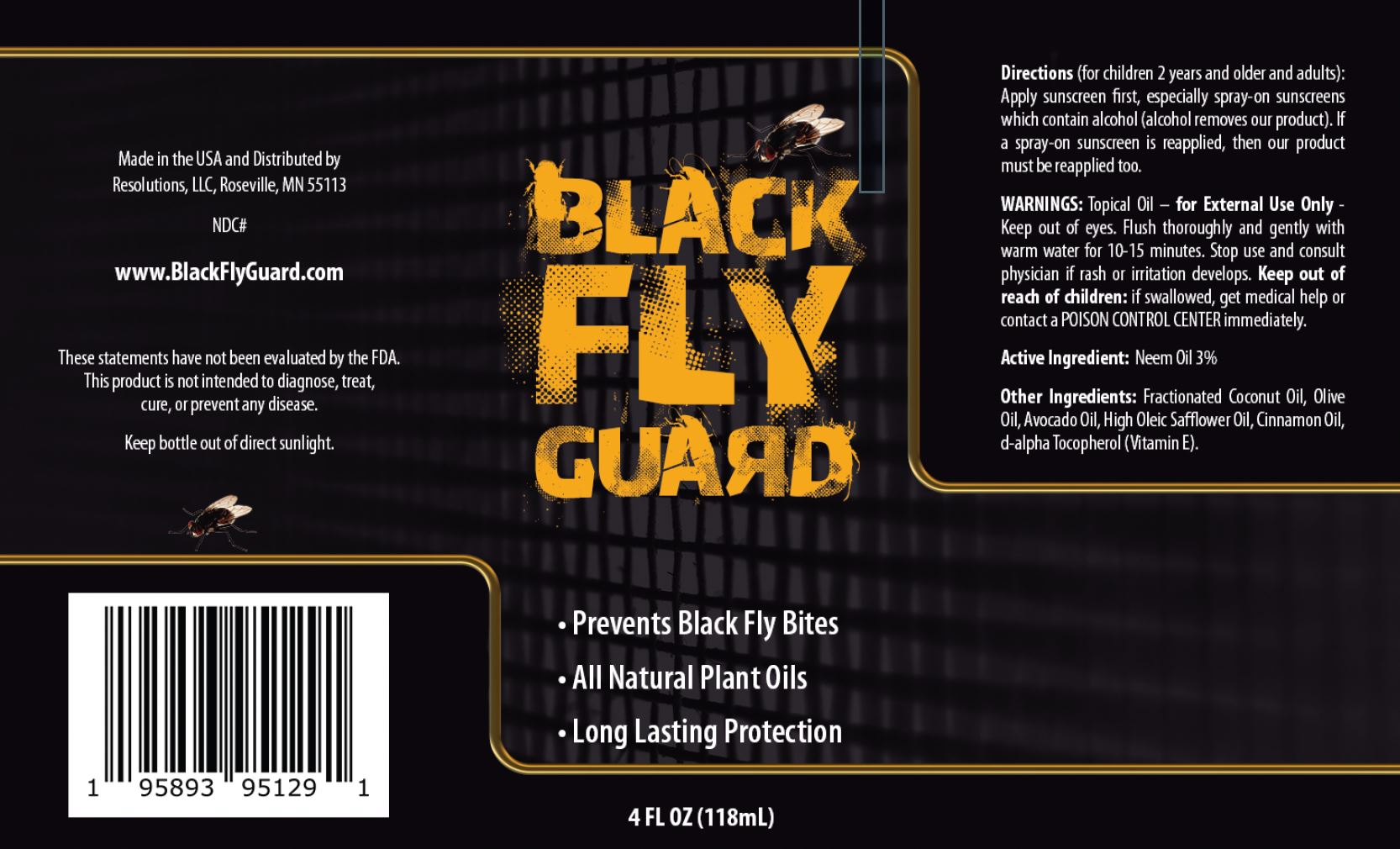 DRUG LABEL: BLACK FLY GUARD
NDC: 63264-201 | Form: OIL
Manufacturer: RESOLUTIONS LLC
Category: homeopathic | Type: HUMAN OTC DRUG LABEL
Date: 20211217

ACTIVE INGREDIENTS: AZADIRACHTA INDICA SEED OIL 3 g/100 mL
INACTIVE INGREDIENTS: MEDIUM-CHAIN TRIGLYCERIDES; OLIVE OIL; AVOCADO OIL; SAFFLOWER OIL; TOCOPHEROL; CINNAMON OIL

RESOLUTIONS - BLACK FLAG GUARD (63264-201)

ACTIVE INGREDIENT

NEEM OIL 3%

PURPOSE

BLACK FLY GUARD

USES

- PREVENTS BLACK FLY BITES
- ALL NATURAL PLANT OILS
- LONG LASTING PROTECTION

WARNINGS

TOPICAL OIL - FOR EXTERNAL USE ONLY - KEEP OUT OF EYES. FLUSH THOROUGHLY AND GENTLY WITH WARM WATER FOR 10-15 MINUTES. STOP USE AND CONSULT PHYSICIAN IF RASH OR IRRITATION DEVELOPS.

KEEP OUT OF REACH OF CHILDREN: IF SWALLOWED, GET MEDICAL HELP OR CONTACT A POISON CONTROL CENTER IMMEDIATELY.

DIRECTIONS

(FOR CHILDREN 2 YEARS AND OLDER AND ADULTS):

APPLY SUNSCREEN FIRST, ESPECIALLY SPRAY-ON SUNSCREENS WHICH CONTAIN ALCOHOL (ALCOHOL REMOVES OUR PRODUCT). IF A SPRAY-ON SUNSCREEN IS REAPPLIED, THEN OUR PRODUCT MUST BE REAPPLIED TOO.

OTHER INGREDIENTS

FRACTIONATED COCONUT OIL, OLIVE OIL, AVOCADO OIL, HIGH OLEIC SAFFLOWER OIL, CINNAMOM OIL, D-ALPHA TOCOPHEROL (VITAMIN E).